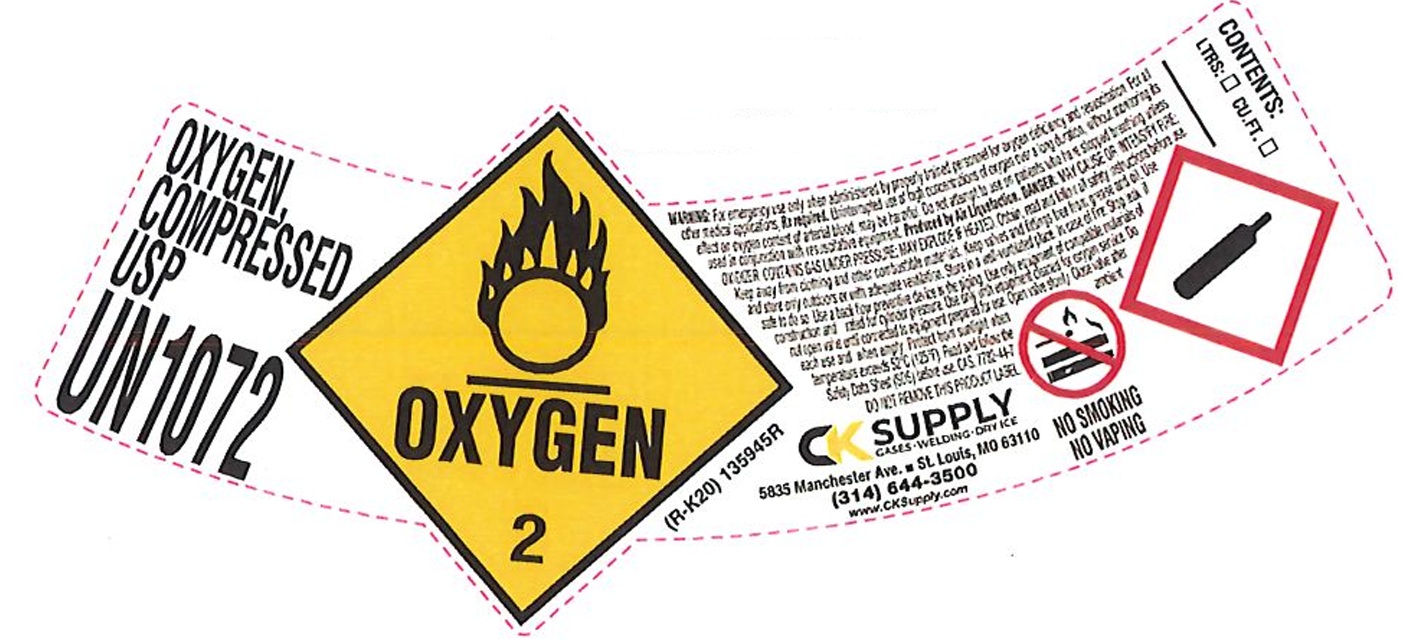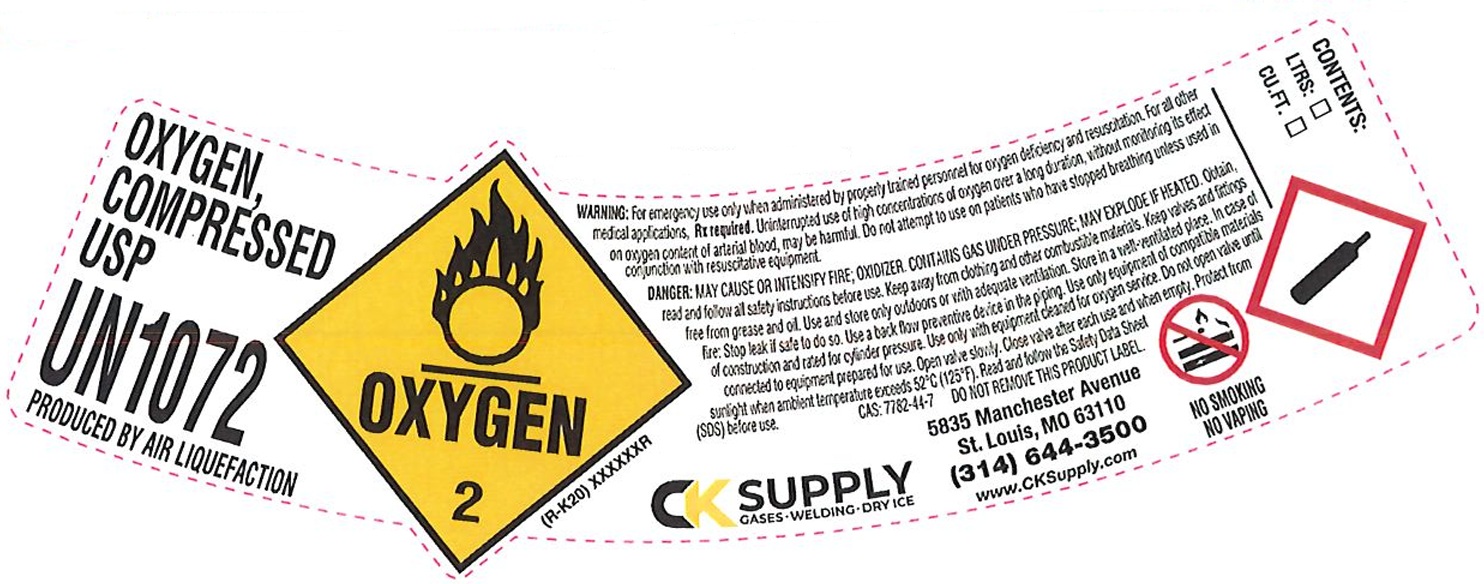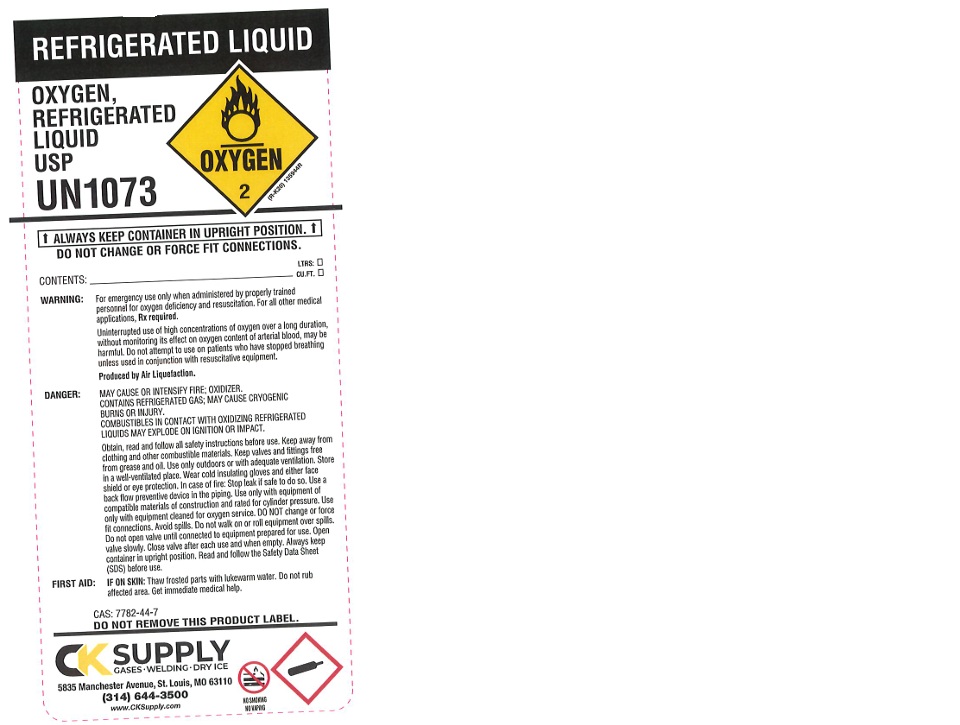 DRUG LABEL: OXYGEN
NDC: 10218-001 | Form: GAS
Manufacturer: CEE-KAY SUPPLY, INC.
Category: prescription | Type: HUMAN PRESCRIPTION DRUG LABEL
Date: 20260225

ACTIVE INGREDIENTS: OXYGEN 995 mL/1 L

OXYGEN

PACKAGE LABEL

OXYGEN, COMPRESSED USP

UN1072

WARNING: For emergency use only when administered by properly trained personnel for oxygen deficiency and resuscitation. For all other medical applications, Rx required. Uninterrupted use of high concentrations of oxygen over a long duration, without monitoring its effect on oxygen content of arterial blood, may be harmful. Do not attempt to use on patients who have stopped breathing unless used in conjunction with resuscitative equipment. Produced by Air Liquefaction. DANGER: MAY CAUSE OR INTENSIFY FIRE; OXIDIZER. CONTAINS GAS UNDER PRESSURE; MAY EXPLODE IF HEATED. Obtain, read and follow all safety instructions before use. Keep away from clothing and other combustible materials. Keep valves and fittings free from grease and oil. Use and store only outdoors or with adequate ventilation. Store in a well-ventilated place. In case of fire: Stop leak if safe to do so. Use a back flow preventive device in the piping. Use only equipment of compatible materials of construction and rated for cylinder pressure. Use only with equipment cleaned for oxygen service. Do not open valve until connected to equipment prepared for use. Open valve slowly. Close valve after each use and when empty. Protect from sunlight when ambient temperature exceeds 52 C (125 F). Read and follow the Safety Data Sheet (SDS) before use. CAS: 7782-44-7

DO NOT REMOVE THIS PRODUCT LABEL

CONTENTS: LTRS: CU.FT

CK SUPPLY CASES WELDING DRY ICE

5835 Manchester Avenue

St. Louis, MO 63110

(314) 644-3500

www.CKSupply.com

NO SMOKING

NO VAPING

PACKAGE LABEL

OXYGEN, COMPRESSED USP

UN1072

PRODUCED BY AIR LIQUEFACTION

WARNING: For emergency use only when administered by properly trained personnel for deficiency and resuscitation. For all other medical applications, Rx required. Uninterrupted use of high concentrations of oxygen over a long duration, without monitoring its effect on oxygen content of arterial blood, may be harmful. Do not attempt to use on patients who have stopped breathing unless used in conjunction with resuscitative equipment.

DANGER: MAY CAUSE OR INTENSIFY FIRE; OXIDIZER. CONTAINS GAS UNDER PRESSURE; MAY EXPLODE IF HEATED. Obtain, read and follow all safety instructions before use. Keep away from clothing and other combustible materials. Keep valves and fittings free from grease and oil. Use and store only outdoors or with adequate ventilation. Store in a well-ventilated place. In case of fire: Stop leak if safe to do so. Use a back flow preventive device in the piping. Use only equipment of compatible materials of construction and rated for cylinder pressure. Use only with equipment cleaned for oxygen service. Do not open valve until connected to equipment prepared for use. Open valve slowly. Close valve after each use and when empty. Protect from sunlight when ambient temperature exceeds 52 C (125 F). Read and follow the Safety Data Sheet (SDS) before use. CAS: 7782-44-7 DO NOT REMOVE THIS PRODUCT LABEL.

CK SUPPLY CASES WELDING DRY ICE

5835 Manchester Avenue

St. Louis, MO 63110

(314) 644-3500

www.CKSupply.com

NO SMOKING

NO VAPING

CONTENTS: LTRS: CU.FT.

PACKAGE LABEL

REFRIGERATED LIQUID

OXYGEN, REFRIGERATED LIQUID USP

UN1073

ALWAYS KEEP CONTAINER IN UPRIGHT POSITION.

DO NOT CHANGE OR FORCE FIT CONNECTIONS.

CONTENTS: LTRS: CU.FT

WARNING: For emergency use only when administered by properly trained personnel for oxygen deficiency and resuscitation. For all other medical applications, Rx required.

Uninterrupted use of high concentrations of oxygen over a long duration, without monitoring its effect on oxygen content of arterial blood, may be harmful. Do not attempt to use on patients who have stopped breathing unless used in conjunction with resuscitative equipment.

Produced by Air Liquefaction.

DANGER: MAY CAUSE OR INTENSIFY FIRE; OXIDIZER. CONTAINS REFRIGERATED GAS: MAY CAUSE CYROGENIC BURNS OR INJURY. COMBUSTIBLES IN CONTACT WITH OXIDIZING REFRIGERATED LIQUIDS MAY EXPLODE ON IGNITION OR IMPACT.

Obtain, read and follow all safety instructions before use. Keep away from clothing and other combustible materials. Keep valves and fittings free from grease and oil. Use only outdoors or with adequate ventilation. Store in a well-ventilated place. Wear cold insulating gloves and either face shield or eye protection. In case of fire: Stop leak if safe to do so. Use a back flow preventive device in the piping. Use only with equipment of compatible materials of construction and rated for cylinder pressure. Use only with equipment cleaned for oxygen service. DO NOT change or force fit connections. Avoid spills. Do not walk on or roll equipment over spills. Do not open valve until connected to equipment prepared for use. Open valve slowly. Close valve after each use and when empty. Always keep container in upright position. Read and follow the Safety Data Sheet (SDS) before use.

FIRST AID: IF ON SKIN: Thaw frosted parts with lukewarm water. Do not rub affected area. Get immediate medical help.

CAS: 7782-44-7

DO NOT REMOVE THIS PRODUCT LABEL.

CK SUPPLY CASES WELDING DRY ICE

5835 Manchester Avenue

St. Louis, MO 63110

(314) 644-3500

www.CKSupply.com

NO SMOKING

NO VAPING